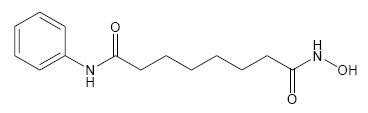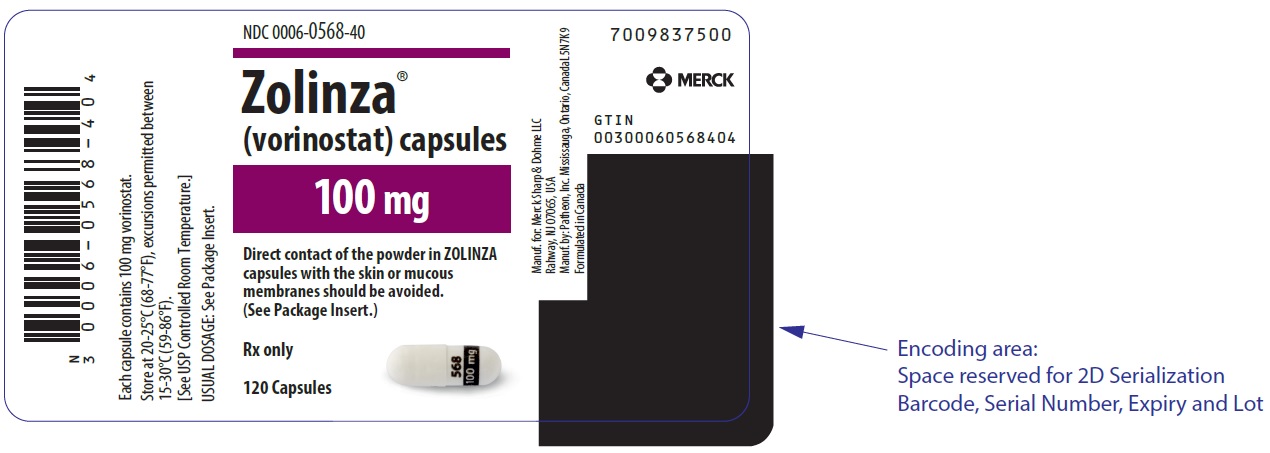 DRUG LABEL: ZOLINZA
NDC: 0006-0568 | Form: CAPSULE
Manufacturer: Merck Sharp & Dohme LLC
Category: prescription | Type: HUMAN PRESCRIPTION DRUG LABEL
Date: 20241112

ACTIVE INGREDIENTS: VORINOSTAT 100 mg/1 1
INACTIVE INGREDIENTS: GELATIN, UNSPECIFIED; MAGNESIUM STEARATE; MICROCRYSTALLINE CELLULOSE; CROSCARMELLOSE SODIUM; SODIUM LAURYL SULFATE; TITANIUM DIOXIDE

HIGHLIGHTS OF PRESCRIBING INFORMATION

These highlights do not include all the information needed to use ZOLINZA safely and effectively. See full prescribing information for ZOLINZA.
ZOLINZA® (vorinostat capsules, for oral use)
Initial U.S. Approval: 2006

1 INDICATIONS AND USAGE

ZOLINZA is a histone deacetylase (HDAC) inhibitor indicated for the treatment of cutaneous manifestations in patients with cutaneous T-cell lymphoma (CTCL) who have progressive, persistent or recurrent disease on or following two systemic therapies. (1)

2 DOSAGE AND ADMINISTRATION

- 400 mg orally once daily with food. (2.1)
- If patient is intolerant to therapy, reduce the dose to 300 mg orally once daily with food. If necessary, reduce the dose further to 300 mg once daily with food for 5 consecutive days each week. (2.2, 5)
- Reduce dose in patients with mild or moderate hepatic impairment. (2.2)

3 DOSAGE FORMS AND STRENGTHS

Capsules: 100 mg (3)

4 CONTRAINDICATIONS

None (4)

5 WARNINGS AND PRECAUTIONS

- Thromboembolism: Monitor for pertinent signs and symptoms of pulmonary embolism and deep vein thrombosis. (5.1)
- Myelosuppression: Thrombocytopenia and anemia may require dose modification or discontinuation. Monitor blood counts every 2 weeks during the first 2 months of therapy and monthly thereafter. (2.2, 5.2, 6)
- Gastrointestinal Toxicity: Nausea, vomiting and diarrhea; patients may require antiemetics, antidiarrheals, and fluid and electrolyte replacement to prevent dehydration. (5.3, 6)
- Hyperglycemia: Monitor blood glucose every 2 weeks during the first 2 months of therapy and monthly thereafter. (5.4)
- Clinical Chemistry Abnormalities: Measure and correct abnormal electrolytes, creatinine, magnesium and calcium at baseline. Monitor every 2 weeks during the first 2 months of therapy and at least monthly during treatment. (5.5)
- Severe Thrombocytopenia with Concomitant Use of other HDAC Inhibitors: Severe thrombocytopenia with gastrointestinal bleeding has been reported with concomitant use of ZOLINZA and other HDAC inhibitors (e.g., valproic acid). Monitor platelet counts more frequently. (5.6, 7.2)
- Embryo-Fetal Toxicity: Fetal harm can occur when administered to a pregnant woman. Women should be apprised of the potential harm to the fetus. (5.7)

6 ADVERSE REACTIONS

- The most common adverse reactions (incidence ≥20%) are diarrhea, fatigue, nausea, thrombocytopenia, anorexia and dysgeusia. (6)

To report SUSPECTED ADVERSE REACTIONS, contact Merck Sharp & Dohme LLC at 1-877-888-4231 or FDA at 1-800-FDA-1088 or www.fda.gov/medwatch .

7 DRUG INTERACTIONS

- Coumarin-derivative anticoagulants: Prolongation of prothrombin time and International Normalized Ratio (INR) have been observed with concomitant use. Monitor INR frequently. (7.1)

8 USE IN SPECIFIC POPULATIONS

- Lactation: Advise women not to breastfeed. (8.2)

FULL PRESCRIBING INFORMATION

1 INDICATIONS AND USAGE

ZOLINZA® is indicated for the treatment of cutaneous manifestations in patients with cutaneous T-cell lymphoma who have progressive, persistent or recurrent disease on or following two systemic therapies.

2 DOSAGE AND ADMINISTRATION

2.1 Dosing Information

The recommended dose is 400 mg orally once daily with food.

Treatment may be continued as long as there is no evidence of progressive disease or unacceptable toxicity.

ZOLINZA capsules should not be opened or crushed [see How Supplied/Storage and Handling (16)].

2.2 Dose Modifications

For Toxicity

If a patient is intolerant to therapy, the dose may be reduced to 300 mg orally once daily with food. The dose may be further reduced to 300 mg once daily with food for 5 consecutive days each week, as necessary.

Hepatic Impairment

Reduce the starting dose to 300 mg orally once daily with food in patients with mild to moderate hepatic impairment (bilirubin 1 to 3 × ULN or AST greater than ULN). There is insufficient evidence to recommend a starting dose for patients with severe hepatic impairment (bilirubin greater than 3 × ULN) [see Use in Specific Populations (8.6) and Clinical Pharmacology (12.3)].

3 DOSAGE FORMS AND STRENGTHS

Capsules: 100 mg white, opaque, hard gelatin capsules with "568" over "100 mg" printed within radial bar in black ink on the capsule body.

4 CONTRAINDICATIONS

None.

5 WARNINGS AND PRECAUTIONS

5.1 Thromboembolism

Pulmonary embolism occurred in 5% (4/86) of patients receiving ZOLINZA, and deep vein thrombosis has also been reported. Monitor for signs and symptoms of these events, particularly in patients with a prior history of thromboembolic events [see Adverse Reactions (6)].

5.2 Myelosuppression

Treatment with ZOLINZA can cause dose-related thrombocytopenia and anemia. Monitor blood counts every 2 weeks during the first 2 months of therapy and monthly thereafter. Adjust dosage or discontinue treatment with ZOLINZA as clinically appropriate [see Dosage and Administration (2.2), Warnings and Precautions (5.6) and Adverse Reactions (6)].

5.3 Gastrointestinal Toxicity

Gastrointestinal disturbances, including nausea, vomiting and diarrhea, have been reported [see Adverse Reactions (6)] and may require the use of antiemetic and antidiarrheal medications. Fluid and electrolytes should be replaced to prevent dehydration [see Adverse Reactions (6.1)]. Pre-existing nausea, vomiting, and diarrhea should be adequately controlled before beginning therapy with ZOLINZA.

5.4 Hyperglycemia

Hyperglycemia has been observed in patients receiving ZOLINZA and was severe in 5% (4/86) of patients [see Adverse Reactions (6.1)]. Monitor serum glucose every 2 weeks during the first 2 months of therapy and monthly thereafter.

5.5 Clinical Chemistry Abnormalities

Obtain chemistry tests, including serum electrolytes, creatinine, magnesium, and calcium, every 2 weeks during the first 2 months of therapy and monthly thereafter. Correct hypokalemia and hypomagnesemia prior to administration of ZOLINZA. Monitor potassium and magnesium more frequently in symptomatic patients (e.g., patients with nausea, vomiting, diarrhea, fluid imbalance or cardiac symptoms).

5.6 Severe Thrombocytopenia when Combined with Other Histone Deacetylase (HDAC) Inhibitors

Severe thrombocytopenia leading to gastrointestinal bleeding has been reported with concomitant use of ZOLINZA and other HDAC inhibitors (e.g., valproic acid). Monitor platelet counts more frequently [see Drug Interactions (7.2)].

5.7 Embryo-Fetal Toxicity

Based on findings from animal studies and its mechanism of action, ZOLINZA can cause fetal harm when administered to a pregnant woman. There are insufficient data on ZOLINZA use in pregnant women to inform a drug-associated risk of major birth defects and miscarriage. In animal reproduction studies, vorinostat crossed the placenta and caused adverse developmental outcomes at exposures approximately 0.5 times the human exposure based on AUC0-24 hours. Advise females of reproductive potential to use effective contraception during treatment and for at least 6 months after the last dose. Advise males with female sexual partners of reproductive potential to use effective contraception during treatment and for at least 3 months after the last dose [see Use in Specific Populations (8.1, 8.3) and Clinical Pharmacology (12.1)].

6 ADVERSE REACTIONS

The following serious adverse reactions have been associated with ZOLINZA in clinical trials and are discussed in greater detail in other sections of the label:

- Thromboembolism [see Warnings and Precautions (5.1)]
- Myelosuppression [see Warnings and Precautions (5.2)]
- Gastrointestinal Toxicity [see Warnings and Precautions (5.3)]
- Hyperglycemia [see Warnings and Precautions (5.4)]
- Clinical Chemistry Abnormalities [see Warnings and Precautions (5.5)]
- Severe thrombocytopenia when combined with other Histone Deacetylase (HDAC) Inhibitors [see Warnings and Precautions (5.6)]

6.1 Clinical Trials Experience

Because clinical trials are conducted under widely varying conditions, adverse reaction rates observed in the clinical trials of a drug cannot be directly compared to rates in the clinical trials of another drug and may not reflect the rates observed in practice.

The safety of ZOLINZA was evaluated in 107 CTCL patients in two single arm clinical studies in which 86 patients received 400 mg once daily.

The data described below reflect exposure to ZOLINZA 400 mg once daily in the 86 patients for a median number of 97.5 days on therapy (range 2 to 480+ days). Seventeen (19.8%) patients were exposed beyond 24 weeks and 8 (9.3%) patients were exposed beyond 1 year. The population of CTCL patients studied was 37 to 83 years of age, 47.7% female, 52.3% male, and 81.4% white, 16.3% black, and 1.2% Asian or multi-racial.

Common Adverse Reactions

The most common drug-related adverse reactions can be classified into 4 symptom complexes: gastrointestinal symptoms (diarrhea, nausea, anorexia, weight decrease, vomiting, constipation), constitutional symptoms (fatigue, chills), hematologic abnormalities (thrombocytopenia, anemia), and taste disorders (dysgeusia, dry mouth). The most common serious drug-related adverse reactions were pulmonary embolism and anemia.

Table 1 summarizes the frequency of CTCL patients with specific adverse reactions, using the National Cancer Institute-Common Terminology Criteria for Adverse Events (NCI-CTCAE, version 3.0).

Table 1: Clinical or Laboratory Adverse Reactions Occurring in CTCL Patients (Incidence ≥10% of patients)
 | ZOLINZA 400 mg once daily (N=86)
Adverse Reactions | All Grades |  | Grades 3-4
 | n | % | n | %
Fatigue | 45 | 52.3 | 3 | 3.5
Diarrhea | 45 | 52.3 | 0 | 0.0
Nausea | 35 | 40.7 | 3 | 3.5
Dysgeusia | 24 | 27.9 | 0 | 0.0
Thrombocytopenia | 22 | 25.6 | 5 | 5.8
Anorexia | 21 | 24.4 | 2 | 2.3
Weight Decreased | 18 | 20.9 | 1 | 1.2
Muscle Spasms | 17 | 19.8 | 2 | 2.3
Alopecia | 16 | 18.6 | 0 | 0.0
Dry Mouth | 14 | 16.3 | 0 | 0.0
Blood Creatinine Increased | 14 | 16.3 | 0 | 0.0
Chills | 14 | 16.3 | 1 | 1.2
Vomiting | 13 | 15.1 | 1 | 1.2
Constipation | 13 | 15.1 | 0 | 0.0
Dizziness | 13 | 15.1 | 1 | 1.2
Anemia | 12 | 14.0 | 2 | 2.3
Decreased Appetite | 12 | 14.0 | 1 | 1.2
Peripheral Edema | 11 | 12.8 | 0 | 0.0
Headache | 10 | 11.6 | 0 | 0.0
Pruritus | 10 | 11.6 | 1 | 1.2
Cough | 9 | 10.5 | 0 | 0.0
Upper Respiratory Infection | 9 | 10.5 | 0 | 0.0
Pyrexia | 9 | 10.5 | 1 | 1.2

The frequencies of more severe thrombocytopenia, anemia [see Warnings and Precautions (5.2)] and fatigue were increased at doses higher than 400 mg once daily of ZOLINZA.

Serious Adverse Reactions

The most common serious adverse reactions in the 86 CTCL patients in two clinical trials were pulmonary embolism reported in 4.7% (4/86) of patients, squamous cell carcinoma reported in 3.5% (3/86) of patients and anemia reported in 2.3% (2/86) of patients. There were single events of cholecystitis, death (of unknown cause), deep vein thrombosis, enterococcal infection, exfoliative dermatitis, gastrointestinal hemorrhage, infection, lobar pneumonia, myocardial infarction, ischemic stroke, pelviureteric obstruction, sepsis, spinal cord injury, streptococcal bacteremia, syncope, T-cell lymphoma, thrombocytopenia and ureteric obstruction.

Discontinuations

Of the CTCL patients who received the 400-mg once daily dose, 9.3% (8/86) of patients discontinued ZOLINZA due to adverse reactions. These adverse reactions, regardless of causality, included anemia, angioneurotic edema, asthenia, chest pain, exfoliative dermatitis, death, deep vein thrombosis, ischemic stroke, lethargy, pulmonary embolism, and spinal cord injury.

Dose Modifications

Of the CTCL patients who received the 400-mg once daily dose, 10.5% (9/86) of patients required a dose modification of ZOLINZA due to adverse reactions. These adverse reactions included increased serum creatinine, decreased appetite, hypokalemia, leukopenia, nausea, neutropenia, thrombocytopenia and vomiting. The median time to the first adverse reactions resulting in dose reduction was 42 days (range 17 to 263 days).

Laboratory Abnormalities

Laboratory abnormalities were reported in all of the 86 CTCL patients who received the 400-mg once-daily dose.

Increased serum glucose was reported as a laboratory abnormality in 69% (59/86) of CTCL patients who received the 400-mg once daily dose; only 4 of these abnormalities were severe (Grade 3). Increased serum glucose was reported as an adverse reaction in 8.1% (7/86) of CTCL patients who received the 400-mg once daily dose [see Warnings and Precautions (5.4)].

Transient increases in serum creatinine were detected in 46.5% (40/86) of CTCL patients who received the 400-mg once daily dose. Of these laboratory abnormalities, 34 were NCI CTCAE Grade 1, 5 were Grade 2, and 1 was Grade 3.

Proteinuria was detected as a laboratory abnormality (51.4%) in 38 of 74 patients tested. The clinical significance of this finding is unknown.

Dehydration

Based on reports of dehydration as a serious drug-related adverse reaction in clinical trials, patients were instructed to drink at least 2 L/day of fluids for adequate hydration [see Warnings and Precautions (5.3, 5.5)].

Adverse Reactions in Non-CTCL Patients

The frequencies of individual adverse reactions were substantially higher in the non-CTCL population. Drug-related serious adverse reactions reported in the non-CTCL population which were not observed in the CTCL population included single events of blurred vision, asthenia, hyponatremia, tumor hemorrhage, Guillain-Barré syndrome, renal failure, urinary retention, cough, hemoptysis, hypertension, and vasculitis.

In patients recovering from bowel surgery and treated perioperatively with ZOLINZA, anastomotic healing complications including fistulas, perforations, and abscess formation have occurred.

7 DRUG INTERACTIONS

7.1 Coumarin-Derivative Anticoagulants

Prolongation of prothrombin time (PT) and International Normalized Ratio (INR) were observed in patients receiving ZOLINZA concomitantly with coumarin-derivative anticoagulants. Physicians should monitor PT and INR more frequently in patients concurrently administered ZOLINZA and coumarin derivatives.

7.2 Other HDAC Inhibitors

Severe thrombocytopenia and gastrointestinal bleeding have been reported with concomitant use of ZOLINZA and other HDAC inhibitors (e.g., valproic acid). Monitor platelet count every 2 weeks for the first 2 months [see Warnings and Precautions (5.6)].

8 USE IN SPECIFIC POPULATIONS

8.1 Pregnancy

Risk Summary

Based on its mechanism of action and findings from animal studies, ZOLINZA can cause fetal harm when administered to a pregnant woman [see Clinical Pharmacology (12.1)].

There are insufficient data on ZOLINZA use in pregnant women to inform a drug-associated risk of major birth defects and miscarriage. In animal reproduction studies, administration of vorinostat to pregnant rats and rabbits during the period of organogenesis caused adverse developmental outcomes at maternal exposures approximately 0.5 times the human exposure based on AUC0-24 hours (see Data). Advise pregnant women of the potential risk to a fetus.

The estimated background risk of major birth defects and miscarriage for the indicated population is unknown. All pregnancies have a background risk of birth defect, loss, or other adverse outcomes. In the U.S. general population, the estimated background risk of major birth defects and miscarriage in clinically recognized pregnancies is 2-4% and 15-20%, respectively.

Data

Animal Data

Results of animal studies indicate that vorinostat crosses the placenta and is found in fetal plasma at levels up to 50% of maternal concentrations. Doses up to 50 and 150 mg/kg/day were tested in rats and rabbits, respectively (~0.5 times the human exposure based on AUC0-24 hours). Treatment-related developmental effects including decreased mean live fetal weights, incomplete ossifications of the skull, thoracic vertebra, sternebra, and skeletal variations (cervical ribs, supernumerary ribs, vertebral count and sacral arch variations) were seen in rats at the highest dose of vorinostat tested. Reductions in mean live fetal weight and an elevated incidence of incomplete ossification of the metacarpals were seen in rabbits dosed at 150 mg/kg/day. The no observed effect levels (NOELs) for these findings were 15 and 50 mg/kg/day (<0.1 times the human exposure based on AUC) in rats and rabbits, respectively. A dose-related increase in the incidence of malformations of the gall bladder was noted in all drug treatment groups in rabbits versus the concurrent control.

8.2 Lactation

Risk Summary

There are no data on the presence of ZOLINZA or its metabolites in human milk, the effects on a breastfed child, or the effects on milk production. Because many drugs are excreted in human milk and because of the potential for serious adverse drug reactions in a nursing child, advise lactating women not to breastfeed during treatment with ZOLINZA and for at least 1 week after the last dose.

8.3 Females and Males of Reproductive Potential

ZOLINZA can cause fetal harm when administered to a pregnant woman [see Warnings and Precautions (5.7) and Use in Specific Populations (8.1)].

Pregnancy Testing

Perform pregnancy testing in females of reproductive potential within 7 days prior to initiating therapy with ZOLINZA.

Contraception

Females

Advise females of reproductive potential to use effective contraception during treatment with ZOLINZA and for at least 6 months after the last dose.

Males

Advise males with female partners of reproductive potential to use effective contraception and to avoid fathering a child during treatment with ZOLINZA and for at least 3 months after the last dose.

Infertility

Based on findings in animals, vorinostat has the potential to affect female fertility [see Nonclinical Toxicology (13.1)].

8.4 Pediatric Use

The safety and effectiveness of ZOLINZA in pediatric patients have not been established.

8.5 Geriatric Use

Clinical studies of ZOLINZA did not include sufficient numbers of subjects aged 65 and over to determine whether they respond differently from younger subjects. Other reported clinical experience has not identified differences in responses between the elderly and younger patients.

8.6 Use in Patients with Hepatic Impairment

ZOLINZA was studied in 42 patients with non-CTCL cancer and varying degrees of hepatic impairment after single and multiple-dose administration. Compared to patients with normal liver function, AUC increases of 50 to 66% were observed in patients with hepatic impairment. The incidence of Grade 3 or 4 thrombocytopenia increased in patients with mild (bilirubin of 1 to 1.5 × ULN and AST < ULN, or bilirubin ≤ ULN and AST > ULN) and moderate (bilirubin 1.5 to ≤ 3 × ULN) hepatic impairment treated daily at doses of 300 and 200 mg respectively.

Patients with severe hepatic impairment (bilirubin > 3 × ULN) have not been treated at doses greater than 200 mg a day. Reduce the initial dose of ZOLINZA in patients with bilirubin 1 to 3 × ULN or AST > ULN [see Dosage and Administration (2.2) and Clinical Pharmacology (12.3)].

10 OVERDOSAGE

No specific information is available on the treatment of overdosage of ZOLINZA.

In the event of overdose, it is reasonable to employ the usual supportive measures, e.g., remove unabsorbed material from the gastrointestinal tract, employ clinical monitoring, and institute supportive therapy, if required. It is not known if vorinostat is dialyzable.

11 DESCRIPTION

ZOLINZA contains vorinostat, which is described chemically as N-hydroxy-N'-phenyloctanediamide.

The empirical formula is C14H20N2O3. The molecular weight is 264.32 and the structural formula is:

Vorinostat is a white to light orange powder. It is very slightly soluble in water, slightly soluble in ethanol, isopropanol and acetone, freely soluble in dimethyl sulfoxide and insoluble in methylene chloride. It has no chiral centers and is non-hygroscopic. The differential scanning calorimetry ranged from 161.7 (endotherm) to 163.9°C. The pH of saturated water solutions of vorinostat drug substance was 6.6. The pKa of vorinostat was determined to be 9.2.

Each 100 mg ZOLINZA capsule for oral administration contains 100 mg vorinostat and the following inactive ingredients: microcrystalline cellulose, sodium croscarmellose and magnesium stearate. The capsule shell excipients are titanium dioxide, gelatin and sodium lauryl sulfate.

12 CLINICAL PHARMACOLOGY

12.1 Mechanism of Action

Vorinostat inhibits the enzymatic activity of histone deacetylases HDAC1, HDAC2 and HDAC3 (Class I) and HDAC6 (Class II) at nanomolar concentrations (IC50<86 nM). These enzymes catalyze the removal of acetyl groups from the lysine residues of proteins, including histones and transcription factors. In some cancer cells, there is an overexpression of HDACs, or an aberrant recruitment of HDACs to oncogenic transcription factors causing hypoacetylation of core nucleosomal histones. Hypoacetylation of histones is associated with a condensed chromatin structure and repression of gene transcription. Inhibition of HDAC activity allows for the accumulation of acetyl groups on the histone lysine residues resulting in an open chromatin structure and transcriptional activation. In vitro, vorinostat causes the accumulation of acetylated histones and induces cell cycle arrest and/or apoptosis of some transformed cells. The mechanism of the antineoplastic effect of vorinostat has not been fully characterized.

12.2 Pharmacodynamics

Cardiac Electrophysiology

A randomized, partially-blind, placebo-controlled, 2-period crossover study was performed to assess the effects of a single 800-mg dose of vorinostat on the QTc interval in 24 patients with advanced cancer. This study was conducted to assess the impact of vorinostat on ventricular repolarization. The upper bound of the 90% confidence interval of the placebo-adjusted mean QTc interval change-from-baseline was less than 10 msec at every time point through 24 hours. Based on these study results, administration of a single supratherapeutic 800-mg dose of vorinostat does not appear to prolong the QTc interval in patients with advanced cancer; however the study did not include a positive control to demonstrate assay sensitivity. In the fasted state, oral administration of a single 800-mg dose of vorinostat resulted in a mean AUC and Cmax and median Tmax of 8.6±5.7 µM∙hr and 1.7±0.67 µM and 2.1 (0.5-6) hours, respectively.

In clinical studies in patients with CTCL, three of 86 CTCL patients exposed to 400 mg once daily had Grade 1 (>450-470 msec) or 2 (>470-500 msec or increase of >60 msec above baseline) clinical adverse reactions of QTc prolongation. In a retrospective analysis of three Phase 1 and two Phase 2 studies, 116 patients had a baseline and at least one follow-up ECG. Four patients had Grade 2 (>470-500 msec or increase of >60 msec above baseline) and 1 patient had Grade 3 (>500 msec) QTc prolongation. In 49 non-CTCL patients from 3 clinical trials who had complete evaluation of QT interval, 2 had QTc measurements of >500 msec and 1 had a QTc prolongation of >60 msec.

12.3 Pharmacokinetics

Absorption

The pharmacokinetics of vorinostat were evaluated in 23 patients with relapsed or refractory advanced cancer. After oral administration of a single 400-mg dose of vorinostat with a high-fat meal, the mean ± standard deviation area under the curve (AUC) and peak serum concentration (Cmax) and the median (range) time to maximum concentration (Tmax) were 5.5±1.8 µM∙hr, 1.2±0.62 µM and 4 (2-10) hours, respectively.

In the fasted state, oral administration of a single 400-mg dose of vorinostat resulted in a mean AUC and Cmax and median Tmax of 4.2±1.9 µM∙hr and 1.2±0.35 µM and 1.5 (0.5-10) hours, respectively. Therefore, oral administration of vorinostat with a high-fat meal resulted in an increase (33%) in the extent of absorption and a modest decrease in the rate of absorption (Tmax delayed 2.5 hours) compared to the fasted state. However, these small effects are not expected to be clinically meaningful. In clinical trials of patients with CTCL, vorinostat was taken with food.

At steady state in the fed-state, oral administration of multiple 400-mg doses of vorinostat resulted in a mean AUC and Cmax and a median Tmax of 6.0±2.0 µM∙hr, 1.2±0.53 µM and 4 (0.5-14) hours, respectively.

Distribution

Vorinostat is approximately 71% bound to human plasma proteins over the range of concentrations of 0.5 to 50 µg/mL.

Metabolism

The major pathways of vorinostat metabolism involve glucuronidation and hydrolysis followed by β-oxidation. Human serum levels of two metabolites, O-glucuronide of vorinostat and 4-anilino-4-oxobutanoic acid were measured. Both metabolites are pharmacologically inactive. Compared to vorinostat, the mean steady state serum exposures in humans of the O-glucuronide of vorinostat and 4-anilino-4-oxobutanoic acid were 4-fold and 13-fold higher, respectively.

In vitro studies using human liver microsomes indicate negligible biotransformation by cytochromes P450 (CYP).

Excretion

Vorinostat is eliminated predominantly through metabolism with less than 1% of the dose recovered as unchanged drug in urine, indicating that renal excretion does not play a role in the elimination of vorinostat. The mean urinary recovery of two pharmacologically inactive metabolites at steady state was 16±5.8% of vorinostat dose as the O-glucuronide of vorinostat, and 36±8.6% of vorinostat dose as 4-anilino-4-oxobutanoic acid. Total urinary recovery of vorinostat and these two metabolites averaged 52±13.3% of vorinostat dose. The mean terminal half-life (t½) was ~2.0 hours for both vorinostat and the O-glucuronide metabolite, while that of the 4-anilino-4-oxobutanoic acid metabolite was 11 hours.

Specific Populations

Gender, Race & Age

Based upon an exploratory analysis of limited data, gender, race and age do not appear to have meaningful effects on the pharmacokinetics of vorinostat.

Pediatric

Vorinostat was not evaluated in patients <18 years of age.

Hepatic Impairment

The single dose pharmacokinetics of a 400 mg ZOLINZA dose was evaluated in patients with non-CTCL cancers with varying degrees of hepatic impairment. The mean AUC of vorinostat in patients with mild (bilirubin > 1 to 1.5 × ULN or AST > ULN but bilirubin ≤ ULN) and moderate (bilirubin 1.5 to ≤ 3 × ULN) hepatic impairment increased by 50% compared to the AUC of vorinostat in patients with normal hepatic function. The mean vorinostat AUC in patients with severe hepatic impairment (bilirubin > 3 × ULN) increased by 66% compared to the AUC of patients with normal hepatic function.

The safety of multiple daily doses of ZOLINZA was also evaluated in patients with non-CTCL cancers with varying degrees of hepatic impairment. The highest dose studied in mild, moderate and severe hepatic impairment was 400, 300 and 200 mg daily respectively. The incidence of Grade 3 or 4 adverse reactions was similar among the hepatic function groups. The most common Grade 3 or 4 adverse reaction was thrombocytopenia.

Reduce the dose in patients with mild to moderate hepatic impairment. There is not enough data in patients with severe hepatic impairment to recommend a dose modification [see Dosage and Administration (2.2) and Use in Specific Populations (8.6)].

Renal Insufficiency

Vorinostat was not evaluated in patients with renal impairment. However, renal excretion does not play a role in the elimination of vorinostat.

Pharmacokinetic Effects of Vorinostat with Other Agents

Vorinostat is not an inhibitor of CYP drug metabolizing enzymes in human liver microsomes at steady state Cmax of the 400 mg dose (Cmax of 1.2 µM vs IC50 of >75 µM). Gene expression studies in human hepatocytes detected some potential for suppression of CYP2C9 and CYP3A4 activities by vorinostat at concentrations higher (≥10 µM) than pharmacologically relevant. Thus, vorinostat is not expected to affect the pharmacokinetics of other agents. As vorinostat is not eliminated via the CYP pathways, it is anticipated that vorinostat will not be subject to drug-drug interactions when co-administered with drugs that are known CYP inhibitors or inducers. However, no formal clinical studies have been conducted to evaluate drug interactions with vorinostat.

In vitro studies indicate that vorinostat is not a substrate of human P-glycoprotein (P-gp). In addition, vorinostat has no inhibitory effect on human P-gp-mediated transport of vinblastine (a marker P-gp substrate) at concentrations of up to 100 µM. Thus, vorinostat is not likely to inhibit P-gp at the pharmacologically relevant serum concentration of 2 µM (Cmax) in humans.

13 NONCLINICAL TOXICOLOGY

13.1 Carcinogenesis, Mutagenesis, Impairment of Fertility

Carcinogenicity studies have not been performed with vorinostat.

Vorinostat was mutagenic in vitro in the bacterial reverse mutation assays (Ames test), caused chromosomal aberrations in vitro in Chinese hamster ovary (CHO) cells and increased the incidence of micro-nucleated erythrocytes when administered to mice (Mouse Micronucleus Assay).

Treatment-related effects on female reproduction were identified in the oral fertility study when females were dosed for 14 days prior to mating through gestational day 7. Doses of 15, 50 and 150 mg/kg/day to rats resulted in approximate exposures of 0.15, 0.36 and 0.70 times the expected clinical exposure based on AUC. Dose-dependent increases in corpora lutea were noted at ≥15 mg/kg/day, which resulted in increased peri-implantation losses at ≥50 mg/kg/day. At 150 mg/kg/day, there were increases in the incidences of dead fetuses and in resorptions.

No effects on reproductive performance or fertility were observed in male rats dosed (20, 50, 150 mg/kg/day; approximate exposures of 0.15, 0.36 and 0.70 times the expected clinical exposure based on AUC) for 70 days prior to mating with untreated females.

14 CLINICAL STUDIES

Cutaneous T-cell Lymphoma

In two open-label clinical studies, patients with refractory CTCL have been evaluated to determine their response rate to oral ZOLINZA. One study was a single-arm clinical study and the other assessed several dosing regimens. In both studies, patients were treated until disease progression or intolerable toxicity.

Study 1

In an open-label, single-arm, multicenter non-randomized study (NCT00091559), 74 patients with advanced CTCL were treated with ZOLINZA at a dose of 400 mg once daily. The primary endpoint was response rate to oral ZOLINZA in the treatment of skin disease in patients with advanced CTCL (Stage IIB and higher) who had progressive, persistent, or recurrent disease on or following two systemic therapies. Enrolled patients should have received, been intolerant to or not a candidate for bexarotene. Extent of skin disease was quantitatively assessed by investigators using a modified Severity Weighted Assessment Tool (SWAT). The investigator measured the percentage total body surface area (%TBSA) involvement separately for patches, plaques, and tumors within 12 body regions using the patient's palm as a "ruler". The total %TBSA for each lesion type was multiplied by a severity weighting factor (1=patch, 2=plaque and 4=tumor) and summed to derive the SWAT score. Efficacy was measured as either a Complete Clinical Response (CCR) defined as no evidence of disease, or Partial Response (PR) defined as a ≥50% decrease in SWAT skin assessment score compared to baseline. Both CCR and PR had to be maintained for at least 4 weeks.

Secondary efficacy endpoints included response duration, time to progression, and time to objective response.

The population had been exposed to a median of three prior therapies (range 1 to 12).

Table 2 summarizes the demographic and disease characteristics of the Study 1 population.

Table 2: Baseline Patient Characteristics (All Patients As Treated)
Characteristics | Vorinostat (N=74)
Age (year)
Mean (SD) | 61.2 (11.3)
Median (Range) | 60.0 (39.0, 83.0)
Gender, n (%)
Male | 38 (51.4%)
Female | 36 (48.6%)
CTCL stage, n (%)
IB | 11 (14.9%)
IIA | 2 (2.7%)
IIB | 19 (25.7%)
III | 22 (29.7%)
IVA | 16 (21.6%)
IVB | 4 (5.4%)
Racial Origin, n (%)
Asian | 1 (1.4%)
Black | 11 (14.9%)
Other | 1 (1.4%)
White | 61 (82.4%)
Time from Initial CTCL Diagnosis (year)
Median (Range) | 2.6 (0.0, 27.3)
Clinical Characteristics
Number of prior systemic treatments, median (range) | 3.0 (1.0, 12.0)

The overall objective response rate was 29.7% (22/74, 95% CI [19.7 to 41.5%]) in all patients treated with ZOLINZA. In patients with Stage IIB and higher CTCL, the overall objective response rate was 29.5% (18/61). One patient with Stage IIB CTCL achieved a CCR. Median times to response were 55 and 56 days (range 28 to 171 days), respectively in the overall population and in patients with Stage IIB and higher CTCL. However, in rare cases it took up to 6 months for patients to achieve an objective response to ZOLINZA.

The median response duration was not reached since the majority of responses continued at the time of analysis, but was estimated to exceed 6 months for both the overall population and in patients with Stage IIB and higher CTCL. When end of response was defined as a 50% increase in SWAT score from the nadir, the estimated median response duration was 168 days and the median time to tumor progression was 202 days.

Using a 25% increase in SWAT score from the nadir as criterion for tumor progression, the estimated median time-to-progression was 148 days for the overall population and 169 days in the 61 patients with Stage IIB and higher CTCL.

Response to any previous systemic therapy does not appear to be predictive of response to ZOLINZA.

Study 2

In an open-label, non-randomized study, ZOLINZA was evaluated to determine the response rate for patients with CTCL who were refractory or intolerant to at least one treatment. In this study, 33 patients were assigned to one of 3 cohorts: Cohort 1, 400 mg once daily; Cohort 2, 300 mg twice daily 3 days/week; or Cohort 3, 300 mg twice daily for 14 days followed by a 7-day rest (induction). In Cohort 3, if at least a partial response was not observed then patients were dosed with a maintenance regimen of 200 mg twice daily. The primary efficacy endpoint, objective response, was measured by the 7-point Physician's Global Assessment (PGA) scale. The investigator assessed improvement or worsening in overall disease compared to baseline based on overall clinical impression. Index and non-index cutaneous lesions as well as cutaneous tumors, lymph nodes and all other disease manifestations were also assessed and included in the overall clinical impression. CCR required 100% clearing of all findings, and PR required at least 50% improvement in disease findings.

The median age was 67.0 years (range 26.0 to 82.0). Fifty-five percent of patients were male, and 45% of patients were female. Fifteen percent of patients had Stage IA, IB, or IIA CTCL and 85% of patients had Stage IIB, III, IVA, or IVB CTCL. The median number of prior systemic therapies was 4 (range 0.0 to 11.0).

In all patients treated, the objective response was 24.2% (8/33) in the overall population, 25% (7/28) in patients with Stage IIB or higher disease and 36.4% (4/11) in patients with Sezary syndrome. The overall response rates were 30.8%, 9.1% and 33.3% in Cohort 1, Cohort 2 and Cohort 3, respectively. The 300 mg twice daily regimen had higher toxicity with no additional clinical benefit over the 400 mg once daily regimen. No CCR was observed.

Among the 8 patients who responded to study treatment, the median time to response was 83.5 days (range 25 to 153 days). The median response duration was 106 days (range 66 to 136 days). Median time to progression was 211.5 days (range 94 to 255 days).

15 REFERENCES

1. "OSHA Hazardous Drugs." OSHA. [http://www.osha.gov/SLTC/hazardousdrugs/index.html]

16 HOW SUPPLIED/STORAGE AND HANDLING

ZOLINZA capsules, 100 mg, are white, opaque hard gelatin capsules with "568" over "100 mg" printed within the radial bar in black ink on the capsule body. They are supplied as follows:

NDC 0006-0568-40.

Each bottle contains 120 capsules.

Storage and Handling

Store at 20-25°C (68-77°F), excursions permitted between 15-30°C (59-86°F) [see USP Controlled Room Temperature].

Procedures for proper handling and disposal of anticancer drugs should be considered. Several guidelines on this subject have been published.^1 There is no general agreement that all of the procedures recommended in the guidelines are necessary or appropriate.

ZOLINZA (vorinostat) capsules should not be opened or crushed. Direct contact of the powder in ZOLINZA capsules with the skin or mucous membranes should be avoided. If such contact occurs, wash thoroughly as outlined in the references. Personnel should avoid exposure to crushed and/or broken capsules [see Nonclinical Toxicology (13.1)].

17 PATIENT COUNSELING INFORMATION

Advise the patient to read the FDA-approved patient labeling (Patient Information).

Patients should be instructed to drink at least 2 L/day of fluid to prevent dehydration and should promptly report excessive vomiting or diarrhea to their physician. Patients should be instructed about the signs of deep vein thrombosis and should consult their physician should any evidence of deep vein thrombosis develop. Patients receiving ZOLINZA should seek immediate medical attention if unusual bleeding occurs. ZOLINZA capsules should not be opened or crushed.

Embryo-Fetal Toxicity

Advise patients that ZOLINZA can cause fetal harm when administered during pregnancy [see Warnings and Precautions (5.7) and Use in Specific Populations (8.1)].

Contraception

Advise females of reproductive potential to use effective contraception during treatment with ZOLINZA and for at least 6 months after the last dose. Advise males with female partners of reproductive potential to use effective contraception and to avoid fathering a child during treatment with ZOLINZA and for at least 3 months after the last dose [see Use in Specific Populations (8.3)].

Lactation

Advise lactating women not to breastfeed during treatment with ZOLINZA and for at least 1 week after the last dose [see Use in Specific Populations (8.2)].

Manuf. for: Merck Sharp & Dohme LLC
Rahway, NJ 07065, USA

Manufactured by:
Patheon, Inc.
Mississauga, Ontario, Canada L5N 7K9

For patent information: www.msd.com/research/patent

Copyright © 2006-2022 Merck & Co., Inc., Rahway, NJ, USA, and its affiliates.
All rights reserved.

uspi-mk0683-c-2207r010

Patient Information
ZOLINZA® (zo LINZ ah)
(vorinostat)
capsules

What is ZOLINZA?

ZOLINZA is a prescription medicine for a type of cancer called cutaneous T-cell lymphoma (CTCL), which is a blood cell cancer that affects your skin. ZOLINZA is used when your CTCL gets worse, does not go away, or comes back after you have taken other medicines.

What you need to know about ZOLINZA

- Before you take this medicine, be sure you understand what it is used for and how to take it safely.
- Keep this information.
- If you have questions about this medicine, ask your doctor or pharmacist.
- Every time you get a refill, look at the Patient Information. There may be new information.

It is not known if ZOLINZA is safe and effective in children.

Should I take ZOLINZA?

Pregnancy

- ZOLINZA has not been studied in pregnant women. It can hurt your baby while you are pregnant.
- Women of childbearing potential (women who can become pregnant and bear children) should use contraception while taking ZOLINZA and for up to 6 months after the last dose. Please speak with your doctor.
- Men who have female partners who can become pregnant and bear children, should use contraception while taking ZOLINZA and for up to 3 months after taking the last dose. Please speak with your doctor.

Breastfeeding

- We do not know if ZOLINZA can pass into breast milk.
- Women should not breastfeed while using ZOLINZA and for up to 1 week after the last dose. Please speak with your doctor.

Diabetes

- If you are taking ZOLINZA and have high blood sugar (hyperglycemia) or diabetes, your doctor may need to change your diet or diabetes medicine to help control your blood sugar.
- Check your blood sugar as often as your doctor tells you to.
- If your blood sugar is higher than normal, call your doctor.
- If you cannot eat or drink like you usually do because you feel sick, vomit, or have diarrhea, call your doctor.

If you have any of these conditions, tell your doctor before taking ZOLINZA:

- a blood clot in your lung (called a Pulmonary Embolus or PE)
- a blood clot in a vein or blood vessel (called Deep Vein Thrombosis or DVT)
- high blood sugar (hyperglycemia) or diabetes
- liver disease
- nausea, vomiting or diarrhea
- any allergies

Are you taking other medicines?

Tell your doctor about all of the medicines you take, including prescription and over-the-counter medicines, vitamins and herbal supplements. Other medicines can affect the way ZOLINZA works.

Your doctor may want to do blood tests more often if you take:

- valproic acid, a medicine for seizures
- a blood thinner, like Coumadin® (warfarin)

How do I take ZOLINZA?

- Take ZOLINZA exactly as prescribed by your doctor.
- Your doctor will tell you how many capsules to take, and when to take them.
- Take with food.
- Drink 8 glasses of water every day (at least 8 ounces each). This will help to keep you hydrated, especially if you have nausea, vomiting or diarrhea.
- Do not chew or break open the capsule. If you break open or crush a capsule, do not touch the capsule or powder. If the powder gets on your skin or in your eyes, wash your skin or eyes with lots of water right away. Then, call your doctor.
- If you cannot swallow the capsule, tell your doctor. You may need a different medicine.

What if I forget to take ZOLINZA?

- If you miss a dose, take it as soon as you remember. If you do not remember until it is almost time for your next dose, just skip the missed dose and take the next dose at your regular time. Do not take two doses of ZOLINZA at the same time.
- If you are not sure what to do, call your doctor.
- If you take more than your prescribed dose, call your doctor, poison center, or emergency room right away.

ZOLINZA may cause serious side effects

If you have any of the following signs or symptoms, tell your doctor right away.

Signs of a blood clot in your legs- Deep Vein Thrombosis or DVT

- Your leg swells up or feels warm
- Your leg hurts or feels very tender

- Your leg hurts when you stand or walk
- Your skin turns red or changes color

Signs of a blood clot in your lungs- Pulmonary Embolus or PE

- You have sudden, sharp chest pain
- You feel short of breath
- You cough up blood
- You start sweating

- Your heart is beating very fast
- You feel like you might pass out
- You feel very anxious

Signs of losing too much fluid from your body- dehydration

You can become dehydrated if you cannot eat or drink like you usually do. This can happen when you feel sick, vomit, or have diarrhea. Call your doctor if you get any of these signs or symptoms:

- Your mouth is dry
- You are sleepier than usual

- Your skin is dry
- You feel dizzy or lightheaded

Changes in your blood

Your doctor will check your blood during treatment with ZOLINZA. Here is a list of some side effects that may mean you have a change in your blood:

- You feel more tired than usual
- You have bleeding or your skin is bruising easily
- You have high blood sugar (you may feel more hungry or thirsty, you may urinate more often than usual)

- You look pale
- You feel short of breath

Common side effects of ZOLINZA

- Diarrhea
- Constipation
- Nausea
- Vomiting

- Not hungry
- Losing weight
- Dry mouth
- Losing hair
- Change in the way things taste

- Muscle aches
- Itchy skin
- Feeling tired
- Feeling dizzy
- Swelling in the foot, ankle, and leg

- Cold
- Cough
- Chills
- Fever
- Headaches

If you have any side effect that bothers you or does not go away, tell your doctor.

There may be other side effects to ZOLINZA that are not listed. For information, ask your doctor or pharmacist. Call your doctor for medical advice about side effects. You may report side effects to FDA at 1-800-FDA-1088.

Where should I keep ZOLINZA?

- Do not let your medicine get really cold or really hot. Keep it at room temperature.
- Keep ZOLINZA and all medicines out of the reach of children.

More information about ZOLINZA

- Medicines are sometimes prescribed for purposes other than those listed in the patient information. Do not use ZOLINZA for a condition for which it was not prescribed. Do not give ZOLINZA to other people, even if they have the same condition. It may harm them.
- This Patient Information summarizes the most important information about ZOLINZA. If you would like more information, talk with your doctor or pharmacist. You can ask them for information about ZOLINZA that was written for healthcare professionals. For more information, call the company that makes ZOLINZA at 1-800-622-4477.

What are the ingredients in ZOLINZA?

The active ingredient is: vorinostat

The inactive ingredients are: microcrystalline cellulose, sodium croscarmellose, magnesium stearate, titanium dioxide, gelatin, and sodium lauryl sulfate.

Merck Sharp & Dohme LLC
Rahway, NJ 07065, USA

Manufactured by: Patheon, Inc., Mississauga, Ontario, Canada L5N 7K9
This Patient Information has been approved by the U.S. Food and Drug Administration.
Revised: 07/2022
For patent information: www.msd.com/research/patent
Copyright © 2006-2022 Merck & Co., Inc., Rahway, NJ, USA, and its affiliates.
All rights reserved.
usppi-mk0683-c-2207r009

PRINCIPAL DISPLAY PANEL - 100 mg Capsule Bottle Label

NDC 0006-0568-40

Zolinza®
(vorinostat) capsules

100 mg

Direct contact of the powder in ZOLINZA
capsules with the skin or mucous
membranes should be avoided.
(See Package Insert.)

Rx only

120 Capsules